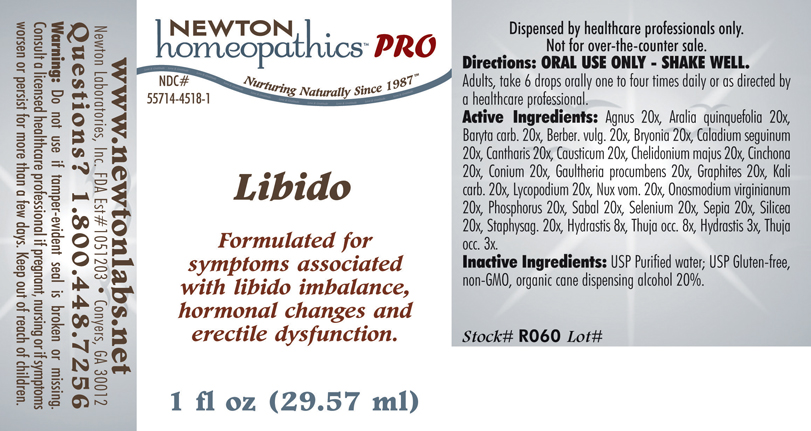 DRUG LABEL: Libido 
NDC: 55714-4518 | Form: LIQUID
Manufacturer: Newton Laboratories, Inc.
Category: homeopathic | Type: HUMAN PRESCRIPTION DRUG LABEL
Date: 20110601

ACTIVE INGREDIENTS: Chaste Tree 20 [hp_X]/1 mL; American Ginseng 20 [hp_X]/1 mL; Barium Carbonate 20 [hp_X]/1 mL; Berberis Vulgaris Root Bark 20 [hp_X]/1 mL; Bryonia Alba Root 20 [hp_X]/1 mL; Dieffenbachia Seguine 20 [hp_X]/1 mL; Lytta Vesicatoria 20 [hp_X]/1 mL; Causticum 20 [hp_X]/1 mL; Chelidonium Majus 20 [hp_X]/1 mL; Cinchona Officinalis Bark 20 [hp_X]/1 mL; Conium Maculatum Flowering Top 20 [hp_X]/1 mL; Gaultheria Procumbens Top 20 [hp_X]/1 mL; Graphite 20 [hp_X]/1 mL; Potassium Carbonate 20 [hp_X]/1 mL; Lycopodium Clavatum Spore 20 [hp_X]/1 mL; Strychnos Nux-vomica Seed 20 [hp_X]/1 mL; Onosmodium Virginianum Root 20 [hp_X]/1 mL; Phosphorus 20 [hp_X]/1 mL; Saw Palmetto 20 [hp_X]/1 mL; Selenium 20 [hp_X]/1 mL; Sepia Officinalis Juice 20 [hp_X]/1 mL; Silicon Dioxide 20 [hp_X]/1 mL; Delphinium Staphisagria Seed 20 [hp_X]/1 mL; Goldenseal 8 [hp_X]/1 mL; Thuja Occidentalis Leafy Twig 8 [hp_X]/1 mL
INACTIVE INGREDIENTS: Alcohol

Libido

INDICATIONS & USAGE SECTION

Libido Formulated for symptoms associated with libido imbalance, hormonal changes and erectile dysfunction.

DOSAGE & ADMINISTRATION SECTION

Directions: ORAL USE ONLY - SHAKE WELL. Adults, take 6 drops orally one to four times daily or as directed by a healthcare professional.

ACTIVE INGREDIENT SECTION

Agnus 20x, Aralia quinquefolia 20x, Baryta carb. 20x, Berber. vulg. 20x, Bryonia 20x, Caladium seguinum 20x, Cantharis 20x, Causticum 20x, Chelidonium majus 20x, Cinchona 20x, Conium 20x, Gaultheria procumbens 20x, Graphites 20x, Kali carb. 20x, Lycopodium 20x, Nux vom. 20x, Onosmodium virginianum 20x, Phosphorus 20x, Sabal 20x, Selenium 20x, Sepia 20x, Silicea 20x, Staphysag. 20x, Hydrastis 8x, Thuja occ. 8x, Hydrastis 3x, Thuja occ. 3x.

PURPOSE SECTION

Formulated for symptoms associated with libido imbalance, hormonal changes and erectile dysfunction.

INACTIVE INGREDIENT SECTION

Inactive Ingredients: USP Purified Water; USP Gluten-free, non-GMO, organic cane dispensing alcohol 20%.

QUESTIONS? SECTION

www.newtonlabs.net Newton Laboratories, Inc. FDA Est # 1051203 - Conyers, GA 30012
Questions? 1.800.448.7256

WARNINGS SECTION

Warning: Do not use if tamper - evident seal is broken or missing. Consult a licensed healthcare professional if pregnant, nursing or if symptoms worsen or persist for more than a few days. Keep out of reach of children.

PREGNANCY OR BREAST FEEDING SECTION

Consult a licensed healthcare professional if pregnant, nursing or if symptoms worsen or persist for more than a few days.

KEEP OUT OF REACH OF CHILDREN SECTION

Keep out of reach of children.